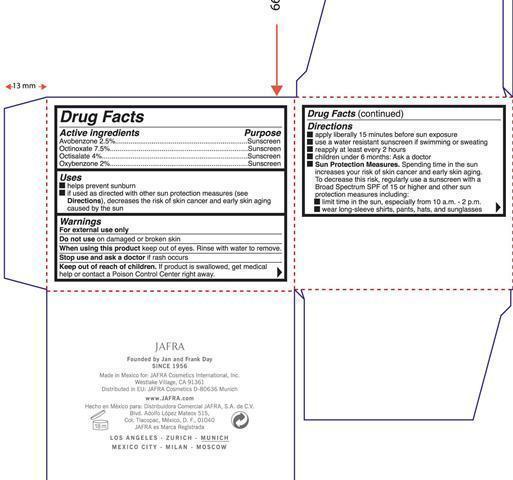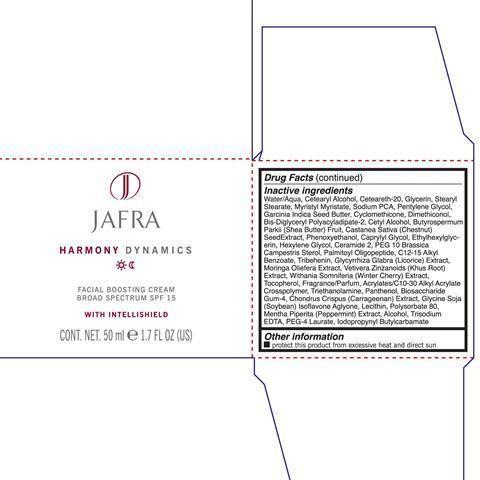 DRUG LABEL: Facial Boosting Broad Spectrum SPF 15

NDC: 68828-159 | Form: CREAM
Manufacturer: JAFRA COSMETICS INTERNATIONAL
Category: otc | Type: HUMAN OTC DRUG LABEL
Date: 20200622

ACTIVE INGREDIENTS: AVOBENZONE 25 mg/1 mL; OCTINOXATE 75 mg/1 mL; OCTISALATE 40 mg/1 mL; OXYBENZONE 20 mg/1 mL
INACTIVE INGREDIENTS: WATER; CETOSTEARYL ALCOHOL; POLYOXYL 20 CETOSTEARYL ETHER; GLYCERIN; STEARYL STEARATE; MYRISTYL MYRISTATE; SODIUM PYRROLIDONE CARBOXYLATE; PENTYLENE GLYCOL; GARCINIA INDICA SEED BUTTER; CYCLOMETHICONE; DIMETHICONOL (2000 CST); CETYL ALCOHOL; SHEA BUTTER; SPANISH CHESTNUT; PHENOXYETHANOL; CAPRYLYL GLYCOL; ETHYLHEXYLGLYCERIN; HEXYLENE GLYCOL; CERAMIDE 2; PALMITOYL OLIGOPEPTIDE; ALKYL (C12-15) BENZOATE; TRIBEHENIN; LICORICE; TOCOPHEROL; CARBOMER INTERPOLYMER TYPE A (ALLYL SUCROSE CROSSLINKED); TROLAMINE; PANTHENOL; CHONDRUS CRISPUS; LECITHIN, SOYBEAN; POLYSORBATE 80; MENTHA PIPERITA; ALCOHOL; EDETATE TRISODIUM; PEG-4 LAURATE; IODOPROPYNYL BUTYLCARBAMATE

Facial Boosting Serum Broad Spectrum SPF 15

Active Ingredients Purpose

Avobenzone 2.5% Sunscreen

Octinoxate 7.5 % Sunscreen

Octisalate 4 % Sunscreen

Oxybenzone 2% Sunscreen

Uses

helps prevents sunburn

if used as directed with other sun protection measures (see Directions), decreases the risk of skin cancer and early skin aging caused by the sun.

Keep out of reach of children. If product is swallowed, get medical help or contact a Poison Control Center right away.

Stop use and ask a doctor if rash occurs.

Warnings

For external use only.

Do not use on damaged or broken skin.

When using this product keep out of eyes. Rinse with water to remove.

Directions

apply liberally 15 minutes before sun exposure

use a water resistant sunscreen if swimming or sweating

reapply at least every 2 hours

children under 6 months: Ask a doctor

Sun Protection Measures. Spending time in the sun increases your risk of skin cancer and early skin aging. To Decrease this risk

Inactive Ingredients
Water/Aqua, Cetearyl Alcohol, Ceteareth-20, Glycerin, Stearyl Stearate, Myristyl Myristate, Sodium PCA, Pentylene Glycol, Garcinia Indica Seed Butter, Cyclomethicone, Dimethiconol, Bis-Diglyceryl Polyacyladipate-2, Cetyl Alcohol, Butyrospermum Parkii (Shea Butter) Fruit, Castanea Sativa (Chestnut) Seed Extract, Phenoxyethanol, Caprylyl Glycol, Ethylhexylglycerin, Hexylene Glycol, Ceramide 2, PEG 10 Brassica Campestris Sterol, Palmitoyl Oligopeptide, C12-15 Alkyl Benzoate, Tribehenin, Glycyrrhiza Glabra (Licorice) Extract, Moringa Oliefera Extract, Vetivera Zinzanoids (Khus Root) Extract, Withania Somnifera (Winter Cherry) Extract, Tocopherol, Fragrance/parfum, Acrylates/C10-30 Alkyl Acrylate Crosspolymer, Triethanolamine, Panthenol, Biosaccharide Gum-4, Chondrus Crispus (Carrageenan) Extract, Glycine Soja (Soybean) Isoflavone Aglycone, Lecithin, Polysorbate 80, Mentha Piperita (peppermint) Extract, Alcohol, Trisodium EDTA, PEG-4 Laurate, Iodopropynyl Butylcarbamate.

PACKAGE LABEL

Jafra

Harmony Dynamics

Facial Boosting Cream Broad Spectrum SPF 15

with intellishield

Cont. Net. 50 ml 1.7 Fl Oz.